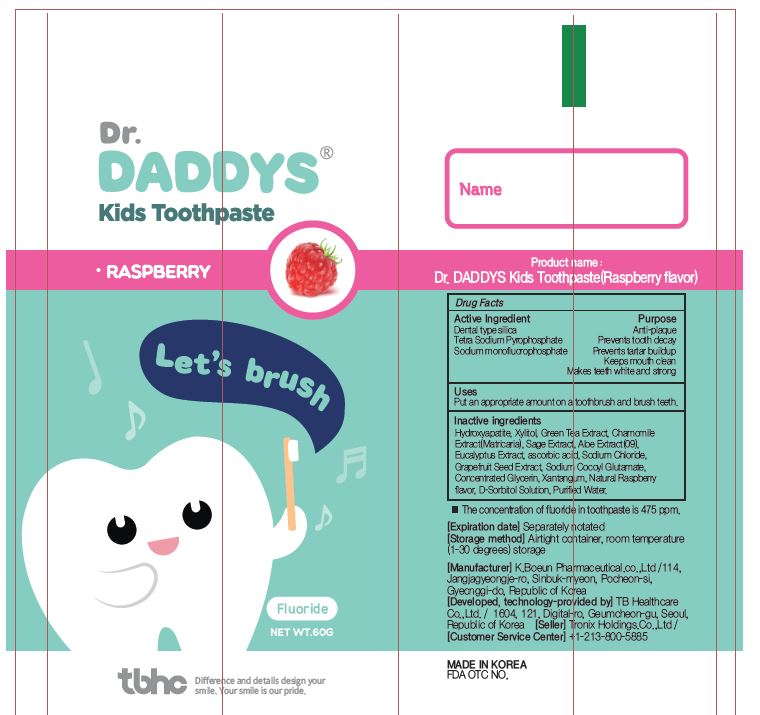 DRUG LABEL: Dr. DADDYS Kids Toothpaste(Raspberry flavor)
NDC: 76884-0011 | Form: PASTE, DENTIFRICE
Manufacturer: TB Healthcare Co., Ltd.
Category: otc | Type: HUMAN OTC DRUG LABEL
Date: 20211013

ACTIVE INGREDIENTS: SILICON DIOXIDE 14 g/100 g; SODIUM PYROPHOSPHATE 0.5 g/100 g; SODIUM MONOFLUOROPHOSPHATE 0.36 g/100 g
INACTIVE INGREDIENTS: XYLITOL; WATER; SODIUM CHLORIDE

ACTIVE INGREDIENT

Silicon Dioxide (Dental Type Silica), Sodium Pyrophosphate (Tetrasodium Pyrophosphate), Sodium Monofluorophosphate

INACTIVE INGREDIENT

D-Sorbitol Solution, Concentrated Glycerin, Xanthangum, Sodium Cocoyl Glutamate, Ascorbic Acid, Hydroxyapatite, Xylitol, Sodium Chloride, Green Tea Extract, Eucalyptus Extract, Matricaria Extract, Aloe Extract, Sage Extract, Grapefruit Seed Extract, natural raspberry flavor, Water

PURPOSE

ANTI-CAVITY

Keep out of reach of children

INDICATIONS AND USAGE

Put an appropriate amount on a toothbrush and brush teeth.

WARNINGS

Storage method

1. Keep it at room temperature in a classified container.

2. Cover and store at room temperature.

3. Store in a not moisture and cool place.

4. Air may come out during use of this product, but there is no problem with its weight.

Usage Precautions

1. Be careful not to swallow. Rinse mouth thoroughly after use

2. If the use of toothpaste causes abnormalities such as gums or mouth injury, discontinue use and consult a doctor or dentist.

3. For children under 6 years of age, use a small amount of toothpaste as small as pea per use, and use under the guidance of a guardian to avoid sucking or swallowing.

4. If a child under 6 years old swallows large amount, consult with a doctor or dentist immediately.

5. Keep out of the reach of children under 6 years of age.

DOSAGE AND ADMINISTRATION

For dental use only